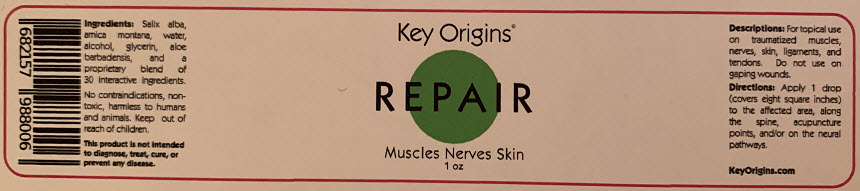 DRUG LABEL: Repair
NDC: 72186-002 | Form: GEL
Manufacturer: Key Origins, Inc.
Category: homeopathic | Type: HUMAN OTC DRUG LABEL
Date: 20191226

ACTIVE INGREDIENTS: Salix Alba Bark 6 [hp_X]/1 mL; Arnica Montana 0.0492 mg/1 mL
INACTIVE INGREDIENTS: Water; Alcohol; Aloe Vera Leaf; Glycerin

Repair

Ingredients

INACTIVE INGREDIENT

Salix alba, arnica montana, water, alcohol, glycerin, aloe barbadensis, and a proprietary blend of 30 interactive homeopathics.

Directions

Apply 1 drop (covers eight square inches) to the affected area or along the spine, acupuncture points and/or the neural pathways.

Descriptions

PURPOSE

For topical use on traumatized muscles, nerves, skin and ligaments and tendons. Do not use on gaping wounds.

No contraindications, nontoxic, harmless to humans and animals.

WARNINGS

Keep out of reach of children.

This product is not intended to diagnose, treat, cure, or prevent any disease.

PRINCIPAL DISPLAY PANEL - 1 oz Jar Label

Key Origins®

REPAIR

Muscles Nerves Skin
1 oz